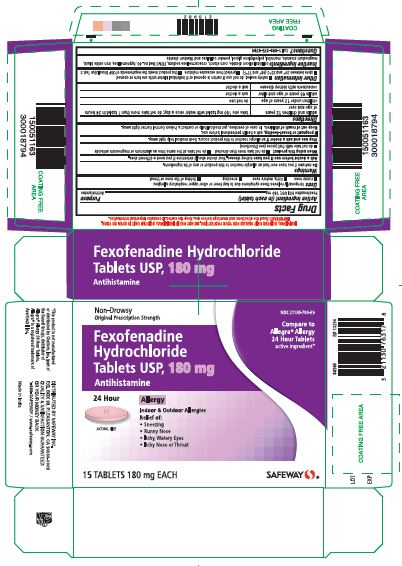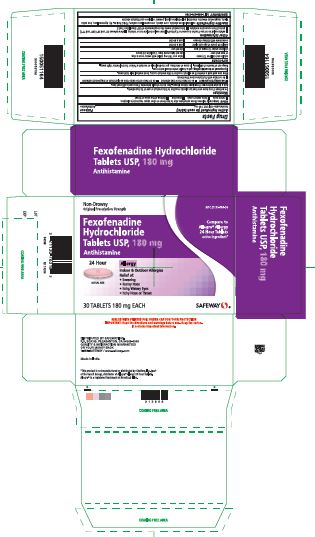 DRUG LABEL: Allergy Relief
NDC: 21130-784 | Form: TABLET
Manufacturer: Safeway Inc
Category: otc | Type: HUMAN OTC DRUG LABEL
Date: 20171211

ACTIVE INGREDIENTS: Fexofenadine Hydrochloride 180 mg/1 1
INACTIVE INGREDIENTS: SILICON DIOXIDE; CROSCARMELLOSE SODIUM; magnesium stearate; mannitol; POWDERED CELLULOSE; FD&C RED NO. 40; HYPROMELLOSE 2910 (6 MPA.S); FERROSOFERRIC OXIDE; polyethylene glycol 400; TITANIUM DIOXIDE; STARCH, CORN

Fexofenadine HCl Tablets USP

Active ingredient(s)

Fexofenadine HCl USP, 180 mg

Purpose

Antihistamine

Use(s)

Allergy

temporarily relieves these symptoms due to hay fever or otherupper respiratory allergies:

- runny nose
- itchy, watery eyes
- sneezing
- itching of the nose or throat

Hives

reduces hives and relieves itching due to hives (urticaria). This product will not prevent hives or an allergic skin reaction from occuring.

Warnings

Hives

Severe Allergic Warning: Get emergency help immediately if you have hives along with any of the following symptom:

- trouble swallowing
- dizziness or loss of consciousness
- swelling of tongue
- swelling in or around mouth
- trouble speaking
- drooling
- wheezing or problems breathing

These symptoms may be signs of anaphylactic shock. This condition canbe life threatening if not treated by a health professional immediately.Symptoms of anaphylactic shock may occur when hives first appear or upto a few hours later.

Not a Substitute for Epinephrine. If your doctor has prescribed an epinephrineinjector for “anaphylaxis” or severe allergy symptoms that could occur withyour hives, never use this product as a substitute for the epinephrine injector.If you have been prescribed an epinephrine injector, you should carry it withyou at all times.

Do not use

Allergy

if you have ever had an allergic reaction to this product or any of its ingredients.

Hives

- to prevent hives from any known cause such as:
  - foods
  - insect stings
  - medicines
  - latex or rubber gloves

because this product will not stop hives from occurring. Avoiding the cause of your hives is the only way to prevent them. Hives can sometimes be serious. If you do not know the cause of your hives, see your doctor for a medical exam. Your doctor may be able to help you find a cause.

- if you have ever had an allergic reaction to this product or any of its ingredients

Ask a doctor before use if you have

Allergy

- kidney disease. Your doctorshould determine if you need a different dose.

Hives

- kidney disease. Your doctor should determine if you need a different dose.
- hives that are an unusual color, look bruised or blistered
- hives that do not itch

When using this product

- do not take more than directed
- do not take at the same time as aluminum or magnesium antacids
- do not take with fruit juices (see Directions)

Stop use and ask doctor if

Allergy

an allergic reaction to this product occurs. Seek medical help right away.

Hives

- an allergic reaction to this product occurs. Seek medical help right away.
- symptoms do not improve after 3 days of treatment
- the hives have lasted more than 6 weeks

If pregnant or breast-feeding

ask a health professional before use.

Keep out of reach of children

In case of overdose, get medical help or contact a Poison Control Center right away.

Directions

180 mg

adults and children 12 years of age and over | take one 180 mg tablet with water once a day; do not take more than 1 tablet in 24 hours
children under 12 years of age | do not use
Adults 65 years of age and older | ask a doctor
consumers with kidney disease | ask a doctor

Other information

safety sealed: do not use if carton is opened or if individual blister units are torn or opened.

Storage

store between 20° - 25°C (68° - 77°F)

protect from excessive moisture

this product meets the requirements of USP Dissolution Test 2.

Inactive ingredients

colloidal silicon dioxide, corn starch, croscarmellose sodium, magnesium stearate, mannitol, and powdered cellulose, opadry pink 03B54504 containing FD&C Red no. 40, hypromellose, iron oxide black, polyethylene glycol and titanium dioxide.

Questions or comments?

call toll-free 1-888-375-3784

Manufactured by:

Dr. Reddy’s Laboratories Limited

Bachupally - 500 090 INDIA

containercarton

Container Carton Label: 30 count

Blister Carton Label: 15 count